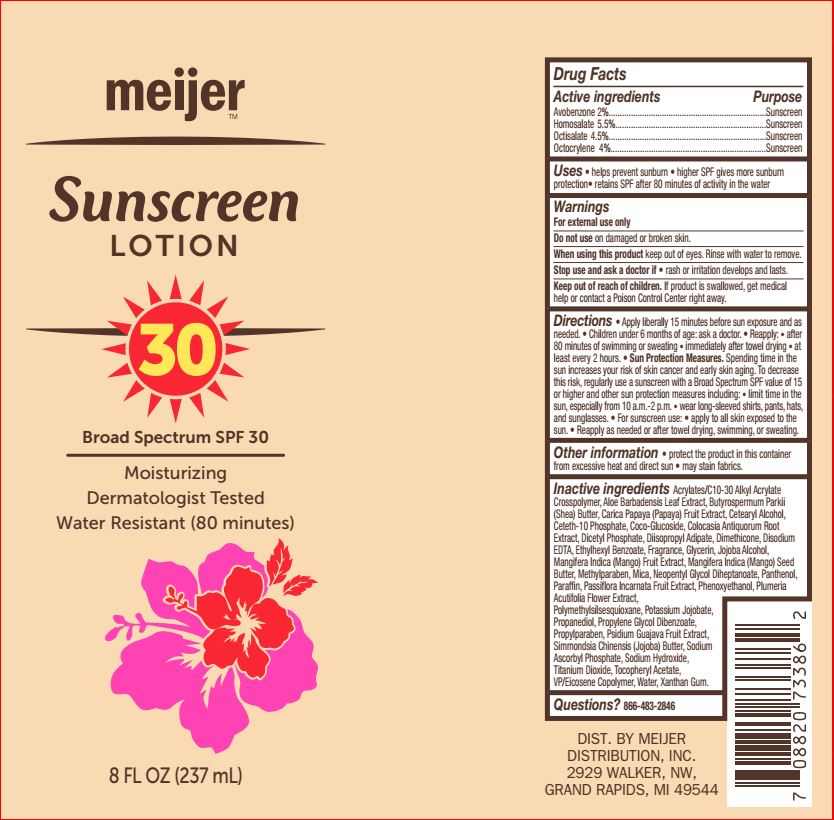 DRUG LABEL: Sunscreen SPF 30
NDC: 41250-794 | Form: LOTION
Manufacturer: Meijer
Category: otc | Type: HUMAN OTC DRUG LABEL
Date: 20180614

ACTIVE INGREDIENTS: Avobenzone 2 g/100 mL; Homosalate 5.5 g/100 mL; Octisalate 4.5 g/100 mL; Octocrylene 4 g/100 mL
INACTIVE INGREDIENTS: CARBOMER INTERPOLYMER TYPE A (ALLYL SUCROSE CROSSLINKED); ALOE VERA LEAF; SHEA BUTTER; PAPAYA; CETOSTEARYL ALCOHOL; Ceteth-10 Phosphate; COCO GLUCOSIDE; COLOCASIA ESCULENTA ROOT; DIHEXADECYL PHOSPHATE; Diisopropyl Adipate; Dimethicone; EDETATE DISODIUM; 2-ETHYLHEXYL BENZOATE; Glycerin; MANGO; MANGIFERA INDICA SEED BUTTER; Methylparaben; Mica; Neopentyl Glycol Diheptanoate; Panthenol; Paraffin; PASSIFLORA INCARNATA FRUIT; PLUMERIA RUBRA FLOWER; Propanediol; Propylene Glycol Dibenzoate; Propylparaben; GUAVA; JOJOBA BUTTER; Sodium Ascorbyl Phosphate; Sodium Hydroxide; Titanium Dioxide; .ALPHA.-TOCOPHEROL ACETATE; EICOSYL POVIDONE; Water; Xanthan Gum

Drug Facts

Active ingredients Purpose
Avobenzone 2%...................................................................Sunscreen
Homosalate 5.5%.................................................................Sunscreen
Octisalate 4.5%....................................................................Sunscreen
Octocrylene 4%.....................................................................Sunscreen

INDICATIONS AND USAGE

Uses • helps prevent sunburn • higher SPF gives more sunburn
protection• retains SPF after 80 minutes of activity in the water

Warnings
For external use only
Do not use on damaged or broken skin.
When using this product keep out of eyes. Rinse with water to remove.
Stop use and ask a doctor if • rash or irritation develops and lasts

Keep out of reach of children. If product is swallowed, get medical
help or contact a Poison Control Center right away

DOSAGE AND ADMINISTRATION

Directions • Apply liberally 15 minutes before sun exposure and as
needed. • Children under 6 months of age: ask a doctor. • Reapply: • after
80 minutes of swimming or sweating • immediately after towel drying • at
least every 2 hours. • Sun Protection Measures. Spending time in the
sun increases your risk of skin cancer and early skin aging. To decrease
this risk, regularly use a sunscreen with a Broad Spectrum SPF value of 15
or higher and other sun protection measures including: • limit time in the
sun, especially from 10 a.m.-2 p.m. • wear long-sleeved shirts, pants, hats,
and sunglasses. • For sunscreen use: • apply to all skin exposed to the
sun. • Reapply as needed or after towel drying, swimming, or sweating.

Other information • protect the product in this container
from excessive heat and direct sun • may stain fabrics.

Inactive ingredients

Acrylates/C10-30 Alkyl Acrylate
Crosspolymer, Aloe Barbadensis Leaf Extract, Butyrospermum Parkii
(Shea) Butter, Carica Papaya (Papaya) Fruit Extract, Cetearyl Alcohol,
Ceteth-10 Phosphate, Coco-Glucoside, Colocasia Antiquorum Root
Extract, Dicetyl Phosphate, Diisopropyl Adipate, Dimethicone, Disodium
EDTA, Ethylhexyl Benzoate, Fragrance, Glycerin, Jojoba Alcohol,
Mangifera Indica (Mango) Fruit Extract, Mangifera Indica (Mango) Seed
Butter, Methylparaben, Mica, Neopentyl Glycol Diheptanoate, Panthenol,
Paraffin, Passiflora Incarnata Fruit Extract, Phenoxyethanol, Plumeria
Acutifolia Flower Extract,
Polymethylsilsesquioxane, Potassium Jojobate,
Propanediol, Propylene Glycol Dibenzoate,
Propylparaben, Psidium Guajava Fruit Extract,
Simmondsia Chinensis (Jojoba) Butter, Sodium
Ascorbyl Phosphate, Sodium Hydroxide,
Titanium Dioxide, Tocopheryl Acetate,
VP/Eicosene Copolymer, Water, Xanthan Gum